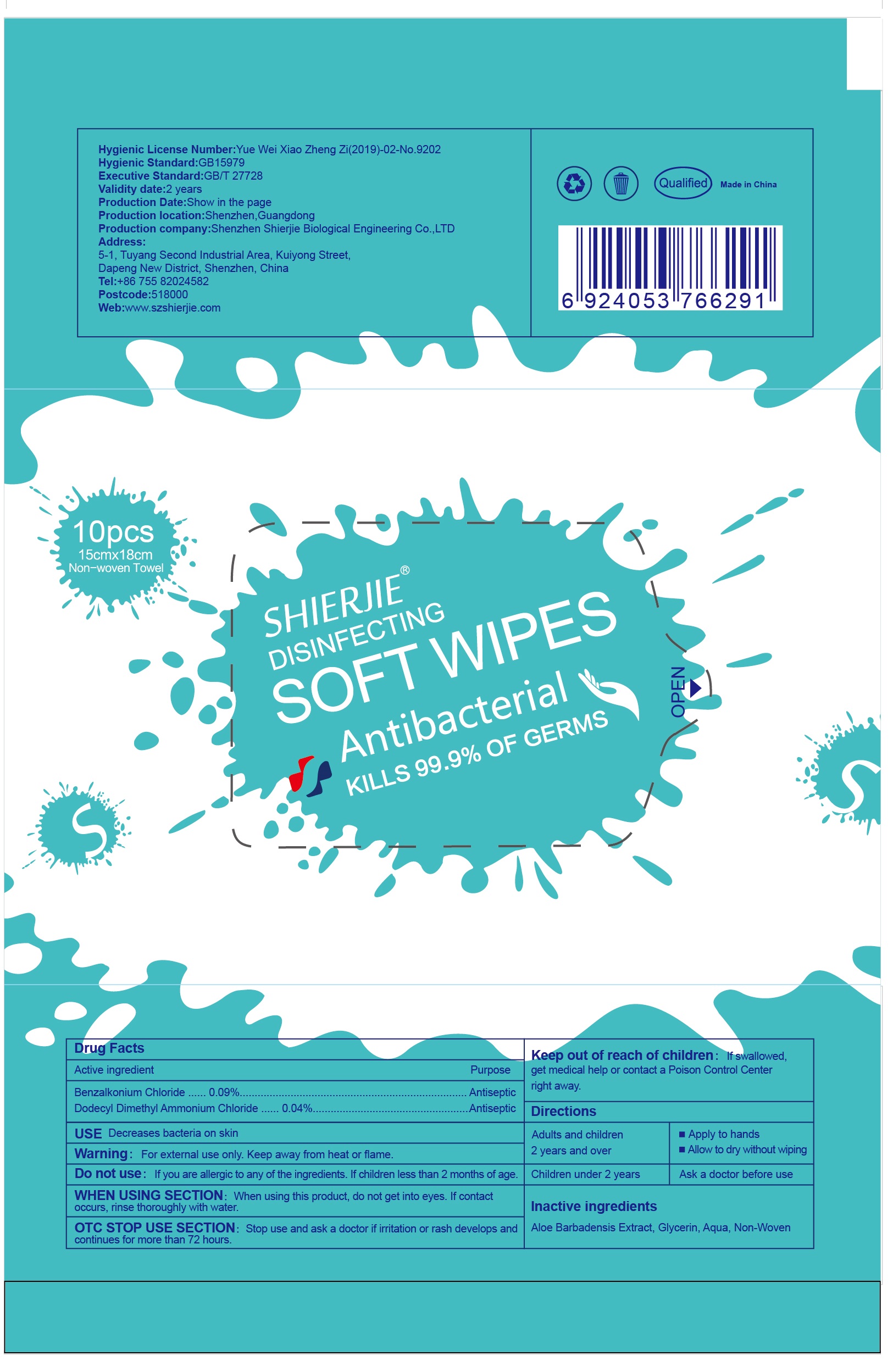 DRUG LABEL: SHIERJIE DISINFECTING SOFT WIPES Antibacterial
NDC: 43116-004 | Form: CLOTH
Manufacturer: Shenzhen Shierjie Biological Engineering Co., LTD
Category: otc | Type: HUMAN OTC DRUG LABEL
Date: 20201221

ACTIVE INGREDIENTS: BENZALKONIUM CHLORIDE 0.09 g/100 1; DIDECYLDIMONIUM CHLORIDE 0.04 g/100 1
INACTIVE INGREDIENTS: ALOE VERA FLOWER; WATER; GLYCERIN

43116-004
SHIERJIE DISINFECTING SOFT WIPES Antibacterial

Active Ingredient

Benzalkonium Chloride 0.09%
Dodecyl Dimethyl Ammonium Chloride 0.04 %

Purpose

Antimicrobial

INDICATIONS AND USAGE

Decreases bacteria on skin

Warnings

For external use only.Keep away from heat or flame.

DO NOT USE

If you are allergic to any of the ingredients.If children less than 2 months of age.

WHEN USING

When using this produc, do not get into eyes.If contact occurs, rinse thoroughly with water.

Stop use and ask a doctor if iri tation or rash develops and continues for more than 72 hours.

KEEP OUT OF REACH OF CHILDREN

If swallowed,get medical help or contact a Poison Control Center right away.

Directions

Adults and children 2 years and over
Apply to hands
Allow to dry without wiping
Children under 2 years
Ask a doctor before use

Other information

/

Inactive ingredients

Aloe Barbadensis Extract , Glycerin , Aqua , Non-woven

Package Label - Principal Display Panel

43116-004-02